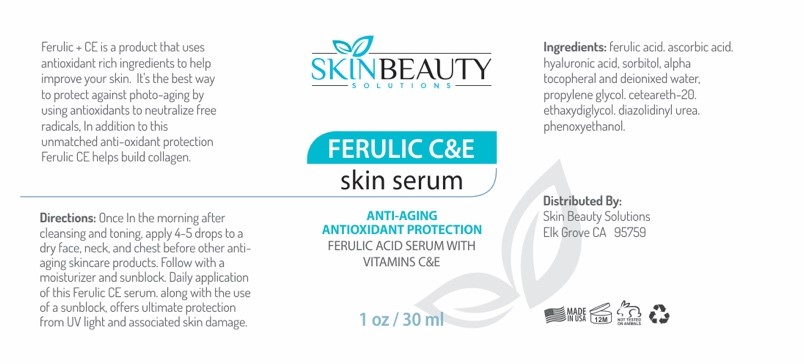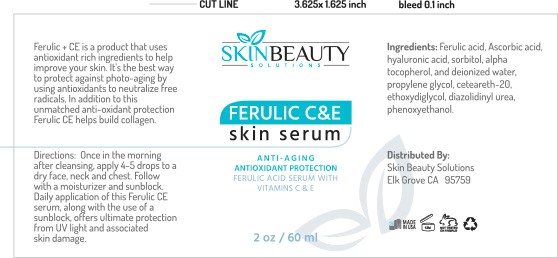 DRUG LABEL: Ferulic Acid CE Skin Serum
NDC: 84785-0052 | Form: SOLUTION
Manufacturer: Gazebo Wellness SKIN LLC
Category: otc | Type: HUMAN OTC DRUG LABEL
Date: 20241218

ACTIVE INGREDIENTS: ASCORBIC ACID 0.3 mg/30 mL; FERULIC ACID 0.3 mg/30 mL; HYALURONIC ACID 0.3 mg/30 mL; .ALPHA.-TOCOPHEROL 0.3 mg/30 mL
INACTIVE INGREDIENTS: DIPROPYLENE GLYCOL; METHOXYDIGLYCOL; CETEARETH-22; WATER; SORBITOL; DIAZOLIDINYL UREA; PHENOXYETHANOL

DOSAGE AND ADMINISTRATION

Directions: Once In the morning after cleansing and toning, apply 4-5 drops to a dry face, neck, and chest before other anti- aging skincare products. Follow with a moisturizer and sunblock. Daily application of this Ferulic CE serum, along with the use of a sunblock offers ultimate protection from UV light and associated skin damage.

WARNINGS

Daily application of this Ferulic CE serum, along with the use of a sunblock offers ultimate protection from UV light and associated skin damage.

INACTIVE INGREDIENT

Inactive ingredients: Sorbitol, Deionized Water, Propylene Glycol, Ceteareth-20, Ethoxydiglycol, Diazolidinyl Urea, Phenoxyethanol.

INDICATIONS AND USAGE

Once In the morning after cleansing and toning, apply 4-5 drops to a dry face, neck, and chest before other anti- aging skincare products. Follow with a moisturizer and sunblock.

keep out of reach of children

PURPOSE

ANTIOXIDANT PROTECTION FERULIC ACID SERUM WITH VITAMINS C&E
1 oz/30 ml
Distributed By:
Skin Beauty Solutions Elk Grove CA 95759

ACTIVE INGREDIENT

Active ingredients: Ferulic Acid, Ascorbic Acid, Hyaluronic Acid, Alpha Tocopherol.

PACKAGE LABEL

Content of labeling